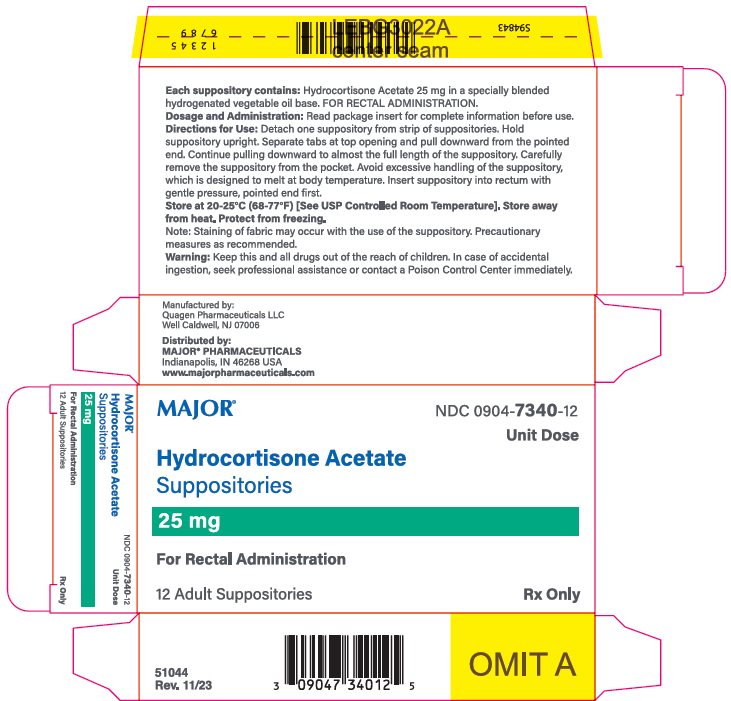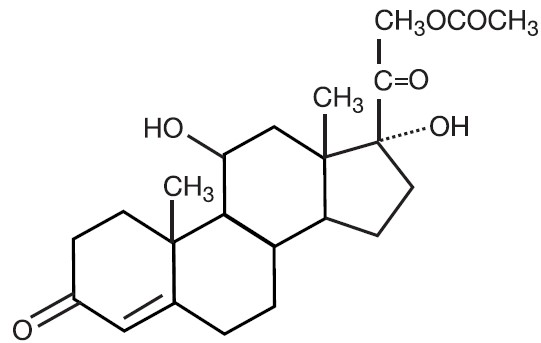 DRUG LABEL: Hydrocortisone Acetate
NDC: 0904-7340 | Form: SUPPOSITORY
Manufacturer: Major Pharmaceuticals
Category: prescription | Type: HUMAN PRESCRIPTION DRUG LABEL
Date: 20250805

ACTIVE INGREDIENTS: HYDROCORTISONE ACETATE 25 mg/1 1
INACTIVE INGREDIENTS: HYDROGENATED PALM KERNEL OIL

Hydrocortisone Acetate Suppositories, 25 mg
For Rectal Administration
Rx only

DESCRIPTION

Hydrocortisone acetate is a corticosteroid designed chemically as pregn-4-ene-3, 20-dione, 21-(acetyloxy)-11, 17-dihydroxy-(11ß) with the following structural formula:

Each suppository for rectal administration contains hydrocortisone acetate, USP 25 mg in a specially blended hydrogenated vegetable base.

CLINICAL PHARMACOLOGY

In normal subjects, about 26% of hydrocortisone acetate is absorbed when the hydrocortisone acetate suppository is applied to the rectum. Absorption of hydrocortisone acetate may vary across abraded or inflamed surfaces.

Topical steroids are primarily effective because of their anti-inflammatory, anti-pruritic and vasoconstrictive action.

INDICATIONS AND USAGE

Hydrocortisone acetate suppositories are indicated for use in inflamed hemorrhoids, post-irradiation (factitial) proctitis, as an adjunct in the treatment of chronic ulcerative colitis, cryptitis, other inflammatory conditions of anorectum, and pruritus ani.

CONTRAINDICATIONS

Hydrocortisone acetate suppositories are contraindicated in those patients having a history of hypersensitivity to hydrocortisone acetate or any of the components.

PRECAUTIONS

Do not use hydrocortisone acetate suppositories unless adequate proctologic examination is made.
If irritation develops, the product should be discontinued and appropriate therapy instituted.
In the presence of an infection, the use of an appropriate antifungal or antibacterial agent should be instituted. If a favorable response does not occur promptly, hydrocortisone acetate should be discontinued until the infection has been adequately controlled.

Carcinogenesis

No long-term studies in animals have been performed to evaluate the carcinogenic potential of corticosteroid suppositories.

INFORMATION FOR PATIENTS

Staining of fabric may occur with use of the suppository. Precautionary measures are recommended.

PREGNANCY CATEGORY C

In laboratory animals, topical steroids have been associated with an increase in the incidence of fetal abnormalities when gestating females have been exposed to rather low dosage levels. There are no adequate and well-controlled studies in pregnant women.
Hydrocortisone acetate suppositories should only be used during pregnancy if the potential benefit justifies the risk of the fetus. Drugs of this class should not be used extensively on pregnant patients, in large amounts, or for prolonged periods of time.
It is not known whether this drug is excreted in human milk, and because many drugs are excreted in human milk and because of the potential for serious adverse reactions in nursing infants from hydrocortisone acetate suppositories, a decision should be made whether to discontinue nursing or to discontinue the drug, taking into account the importance of the drug to the mother.

ADVERSE REACTIONS

The following local adverse reactions have been reported with hydrocortisone acetate suppositories; burning, itching, irritation, dryness, folliculitis, hypopigmentation, allergic contact dermatitis, secondary infection.
To report an adverse event, please contact Rising Pharma Holdings, Inc. at 1-844-874-7464, or FDA at 1-800-FDA-1088 or www.fda.gov/medwatch.

Drug abuse and dependence have not been reported in patients treated with hydrocortisone acetate suppositories.

OVERDOSAGE

If signs and symptoms of systemic overdosage occur, discontinue use.

DOSAGE AND ADMINISTRATION

For rectal administration. Detach one suppository from strip of suppositories. Hold suppository upright. Separate tabs at top opening and pull downward from the pointed end. Continue pulling downward to almost the full length of the suppository. Carefully remove the suppository from the pocket. Avoid excessive handling of the suppository which is designed to melt at body temperature. Insert suppository into the rectum with gentle pressure, pointed end first. Insert one suppository in the rectum twice daily, morning and night for two weeks, in nonspecific proctitis. In more severe cases, one suppository three times a day or two suppositories twice daily. In factitial proctitis, the recommended duration of therapy is six to eight weeks or less, according to the response of the individual case.

HOW SUPPLIED

Hydrocortisone acetate suppositories 25 mg are white to off-white, smooth surfaced and bullet shaped with one pointed end.
Carton of 12 suppositories, NDC 0904-7340-12

Carton of 24 suppositories, NDC 0904-7340-24

STORAGE

Store at 20°-25°C (68°-77°F) [See USP Controlled Room Temperature]. Excursions permitted to 15°-30°C (59°-86°F). Store away from heat. Protect from freezing. Avoid contact with eyes.
KEEP THIS AND ALL DRUGS OUT OF THE REACH OF CHILDREN. In case of accidental ingestion, seek professional assistance or contact a Poison Control Center immediately.
Rx Only
Manufactured by:
Quagen Pharmaceuticals LLC
West Caldwell, NJ 07006

Distributed By:

MAJOR® PHARMACEUTICALS

Indianapolis, IN 46268 USA

52030
Rev.01/21

Package/Label Display Panel

Hydrocortisone Acetate Suppositories

25 mg

12 Adult Suppositories